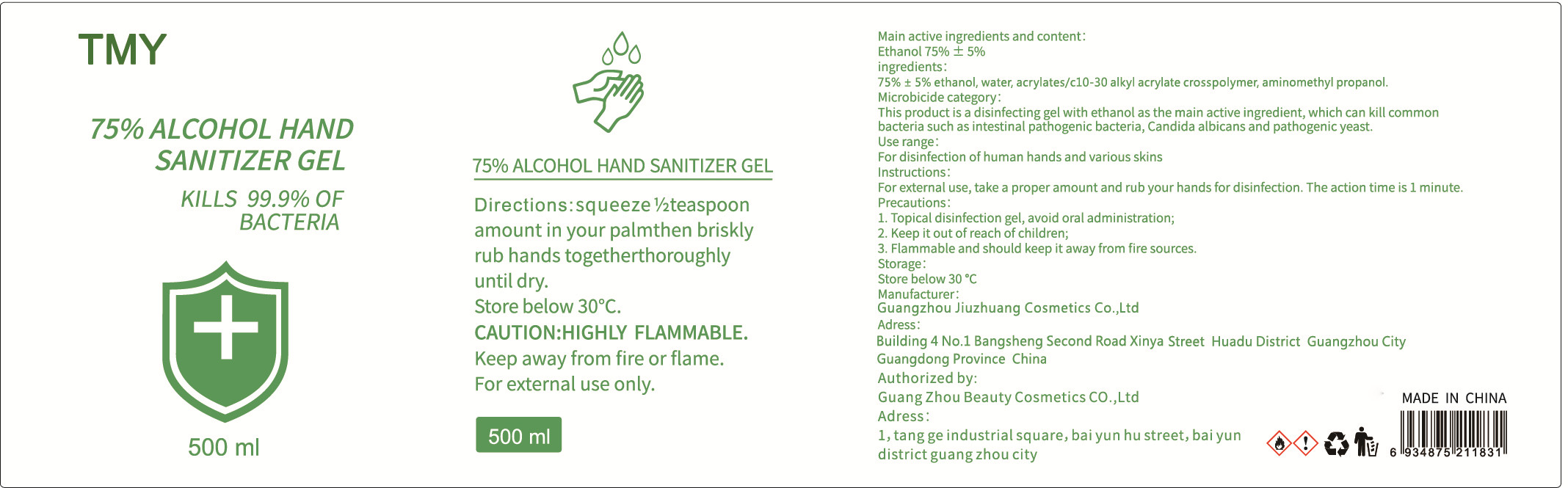 DRUG LABEL: 75% ALCOHOL HAND SANITIZERGEL
NDC: 40303-007 | Form: GEL
Manufacturer: Guangzhou Beauty Cosmetics Co., Ltd.
Category: otc | Type: HUMAN OTC DRUG LABEL
Date: 20200810

ACTIVE INGREDIENTS: ALCOHOL 375 mL/500 mL
INACTIVE INGREDIENTS: CARBOMER INTERPOLYMER TYPE A (55000 CPS); WATER; AMINOMETHYLPROPANOL

DOSAGE AND ADMINISTRATION

Store below 30 °C

INACTIVE INGREDIENT

water,acrylates/c10-30 alkyl acrylate crosspolymer,aminomethyl propanol

INDICATIONS AND USAGE

For external use, take a proper amount and rub your hands for disinfection. The action time is 1 minute.

ACTIVE INGREDIENT

ethanol

keep out of children

PURPOSE

Disinfection
Sterilization
No Rinseing

WARNINGS

1. Topical disinfection gel, avoid oral administration;
2. Keep it out of reach of children;
3. Flammable and should keep it away from fire sources.